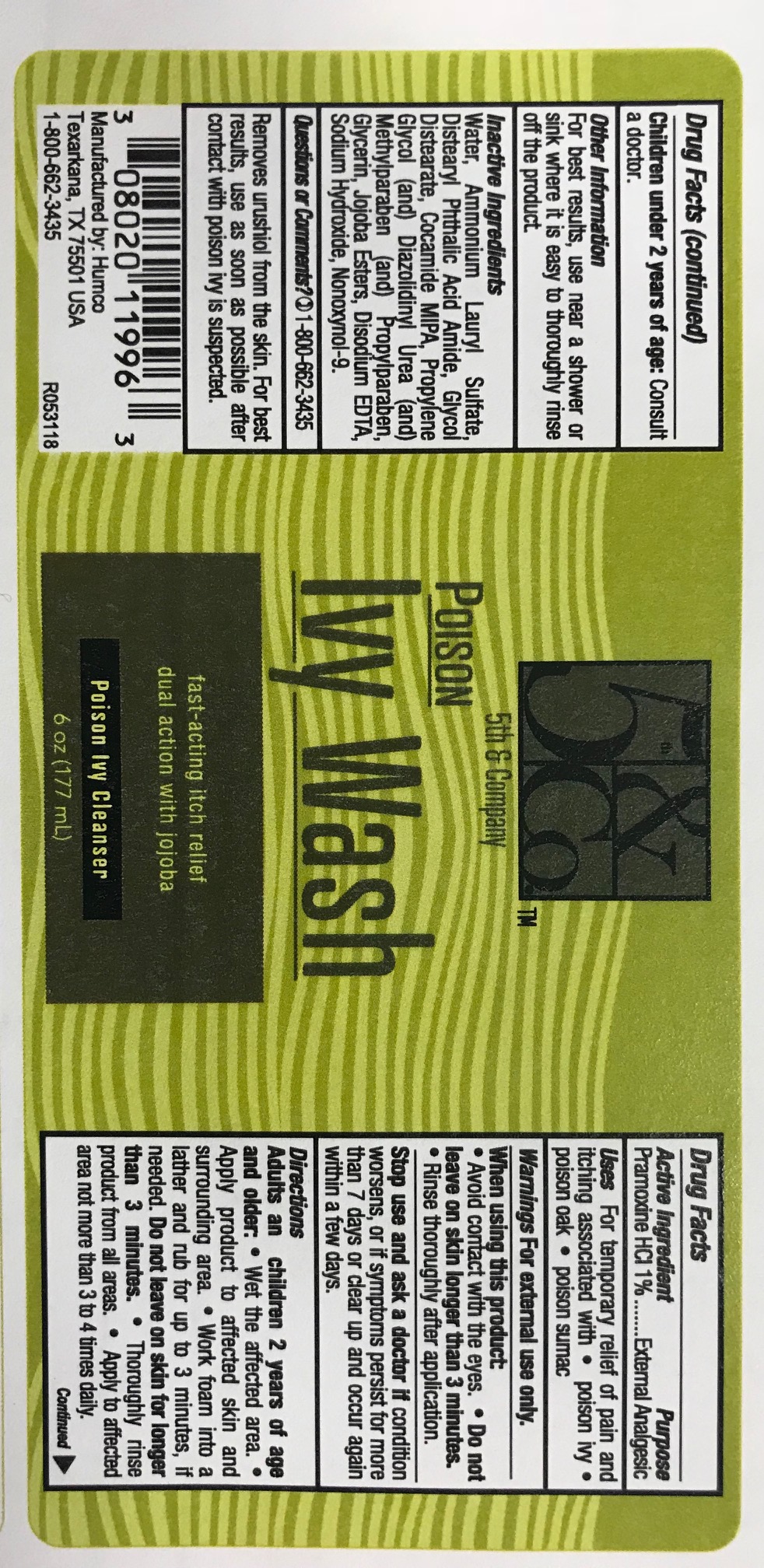 DRUG LABEL: Private Label Poison Ivy Wash
NDC: 0802-0119 | Form: LOTION
Manufacturer: Humco Holding Group, Inc.
Category: otc | Type: HUMAN OTC DRUG LABEL
Date: 20200620

ACTIVE INGREDIENTS: PRAMOXINE HYDROCHLORIDE 1 mg/1 mg
INACTIVE INGREDIENTS: METHYLPARABEN; GLYCERIN; HYDROLYZED JOJOBA ESTERS (ACID FORM); EDETATE DISODIUM; NONOXYNOL-9; AMMONIUM LAURYL SULFATE; PROPYLPARABEN; GLYCOL DISTEARATE; PROPYLENE GLYCOL; DIAZOLIDINYL UREA; SODIUM HYDROXIDE; WATER

5th & Co. Poison Ivy Wash

Drug Facts

Active Ingredient

Pramoxine HCl 1%

Purpose

External analgesic

Uses

For temporary relief of pain and itching associated with poison ivy, poison oak, and poison summac

Warnings

For external use only

When using this product

Avoid contact with the eyes. Do not leave on skin longer than three minutes. Rinse throughly after application.

Stop use and ask a doctor if

conditions worsen or if symptoms persist for more than 7 days or clear up and occur again within a few days.

Directions

Adult and children 2 years of age and older. Wet affected areas. Apply the product to affected skin and surrounding area. Work foam into a lather and rub for up to 3 minutes, if needed. Do not leave on skin for longer than 3 minutes. Thoughly rinse product from all areas. Apply to affected are not more than 3 to 4 times daily. Children under 2 years of age. Consult a doctor.

Other Information

For best results, use near a shower or sink where it is easy to thoughly rinse off product.

Inactive Ingredients

Water, Ammonium Laurl Sulfate, Distearyl Phtalic Acid Amide, Glyco Distearate, Cocamide MIPA, Propylene Glycol, (and) Diazodinyl Urea (and) Methylparaben (and) Propylparaben, Glycerin, Jojoba Esters, Disodium EDTA, Sodium Hydroxide, Nonoxynol-9.

Questions or Comments?

1-800-662-3435

Removes Urushiol from the skin. For best results, use as soon as possible after contact with poison ivy is suspected.